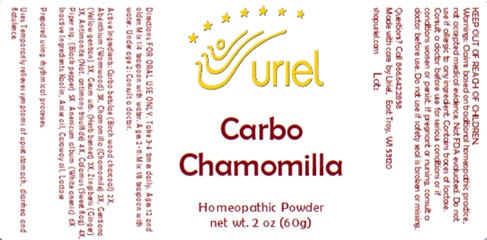 DRUG LABEL: Carbo Chamomilla
NDC: 48951-3257 | Form: POWDER
Manufacturer: Uriel Pharmacy Inc
Category: homeopathic | Type: HUMAN OTC DRUG LABEL
Date: 20241115

ACTIVE INGREDIENTS: GEUM URBANUM ROOT 3 [hp_X]/1 g; BLACK PEPPER 5 [hp_X]/1 g; GINGER 3 [hp_X]/1 g; ANTIMONY TRISULFIDE 4 [hp_X]/1 g; ARSENIC TRIOXIDE 6 [hp_X]/1 g; ACORUS CALAMUS ROOT 4 [hp_X]/1 g; ACTIVATED CHARCOAL 2 [hp_X]/1 g; WORMWOOD 3 [hp_X]/1 g; MATRICARIA RECUTITA 3 [hp_X]/1 g; GENTIANA LUTEA ROOT 3 [hp_X]/1 g
INACTIVE INGREDIENTS: LACTOSE, UNSPECIFIED FORM; KAOLIN; ANISE OIL; CARAWAY OIL

Carbo Chamomilla

INDICATIONS AND USAGE

Directions: FOR ORAL USE ONLY.

DOSAGE AND ADMINISTRATION

Take 3-4 times daily. Ages 12 and older: Mix 1/4 teaspoon with water. Ages 2-11: Mix 1/8 teaspoon with water. Under age 2: Consult a doctor.

ACTIVE INGREDIENT

Active Ingredients: Carbo betulae (Birch wood charcoal) 2X, Absinthium (Wormwood) 3X, Chamomilla (Chamomile) 3X, Gentiana (Yellow gentian) 3X, Geum urb. (Herb bennet) 3X, Zingiberis (Ginger) 3X, Antimonite (Nat. antimony trisulfide) 4X, Calamus (Sweet flag) 4X, Piper nig. (Black pepper) 5X Arsenicum album (White arsenic) 6X

Inactive Ingredients: Kaolin, Anise oil, Caraway oil, Lactose

Prepared using rhythmical processes.

PURPOSE

Uses: Temporarily relieves symptoms of upset stomach, diarrhea and flatulence.

KEEP OUT OF REACH OF CHILDREN.

WARNINGS

Warnings: Claims based on traditional homeopathic practice, not accepted medical evidence. Not FDA evaluated. Do not use if allergic to any ingredient. Contains traces of lactose. Consult a doctor before use for serious conditions or if conditions worsen or persist. If pregnant or nursing, consult a doctor before use. Do not use if safety seal is broken or missing.

Questions? Call 866.642.2858
Made with care by Uriel, East Troy, WI 53120
shopuriel.com Lot: